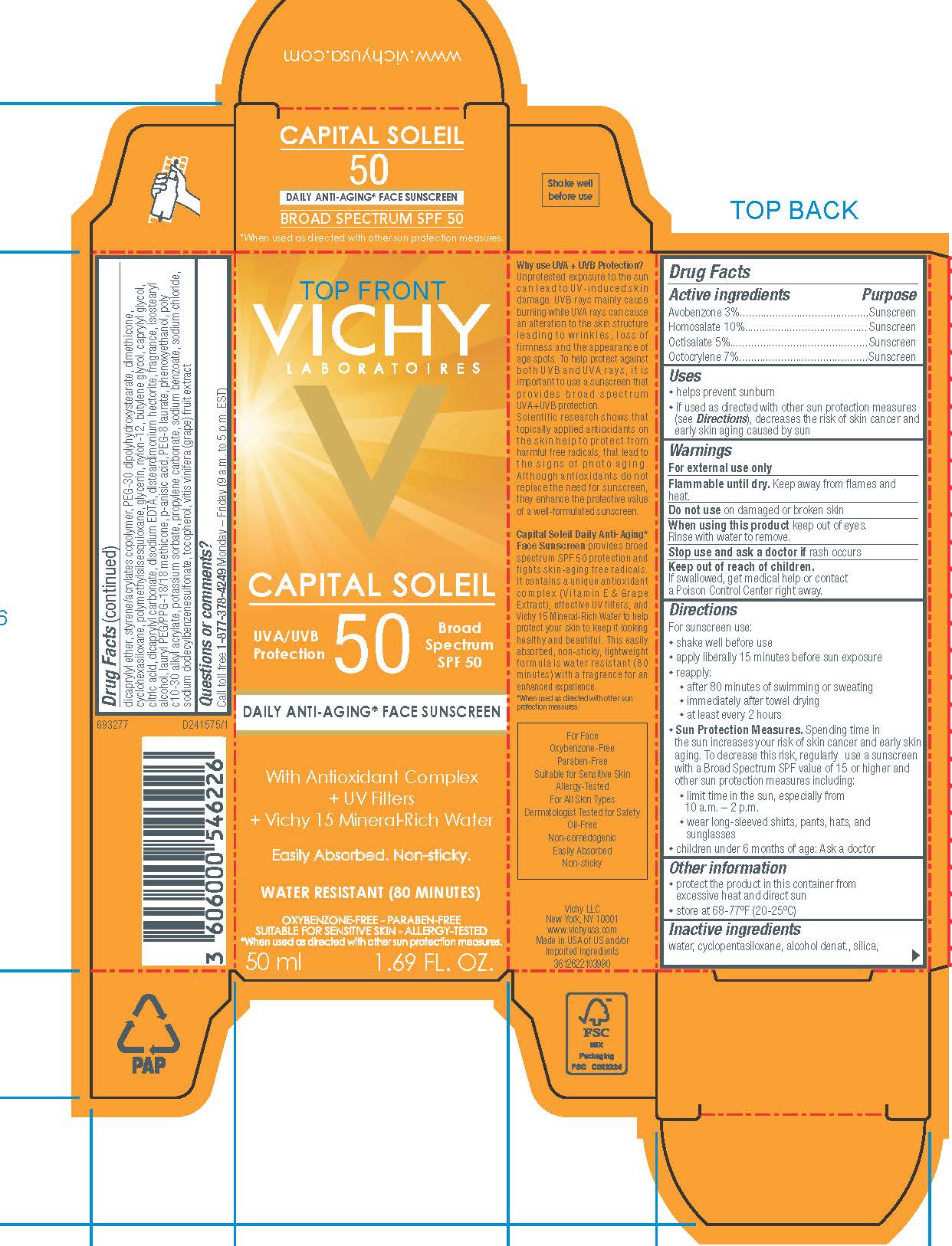 DRUG LABEL: Vichy Laboratoires Capital Soleil 50 Daily AntiAging Face Sunscreen Broad Spectrum SPF 50 Water Resistant 80 Minutes
NDC: 49967-054 | Form: LOTION
Manufacturer: L’Oreal USA Products Inc
Category: otc | Type: HUMAN OTC DRUG LABEL
Date: 20241230

ACTIVE INGREDIENTS: AVOBENZONE 30 mg/1 mL; HOMOSALATE 100 mg/1 mL; OCTISALATE 50 mg/1 mL; OCTOCRYLENE 70 mg/1 mL
INACTIVE INGREDIENTS: WATER; CYCLOMETHICONE 5; ALCOHOL; SILICON DIOXIDE; DICAPRYLYL ETHER; STYRENE/ACRYLAMIDE COPOLYMER (500000 MW); PEG-30 DIPOLYHYDROXYSTEARATE; DIMETHICONE; CYCLOMETHICONE 6; POLYMETHYLSILSESQUIOXANE (4.5 MICRONS); GLYCERIN; NYLON-12; BUTYLENE GLYCOL; CAPRYLYL GLYCOL; CITRIC ACID MONOHYDRATE; EDETATE DISODIUM; DISTEARDIMONIUM HECTORITE; ISOSTEARYL ALCOHOL; LAURYL PEG/PPG-18/18 METHICONE; P-ANISIC ACID; PEG-8 LAURATE; PHENOXYETHANOL; POTASSIUM SORBATE; PROPYLENE CARBONATE; SODIUM BENZOATE; SODIUM CHLORIDE; SODIUM DODECYLBENZENESULFONATE; TOCOPHEROL; WINE GRAPE

Drug Facts

Active ingredients

Avobenzone 3%

Homosalate 10%

Octisalate 5%

Octocrylene 7%

Purpose

Sunscreen

Uses

- helps prevent sunburn
- if used as directed with other sun protection measures (see Directions), decreases the risk of skin cancer and early skin aging caused by the sun

Warnings

For external use only

Flammable until dry.

Keep away from flames and heat.

Do not use

on damaged or broken skin

When using this product

keep out of eyes. Rinse with water to remove.

Stop use and ask a doctor if

rash occurs

Keep out of reach of children.

If swallowed, get medical help or contact a Poison Control Center right away.

Directions

For sunscreen use:

● apply liberally 15 minutes before sun exposure

● reapply:

● after 80 minutes of swimming or sweating

● immediately after towel drying

● at least every 2 hours

● Sun Protection Measures. Spending time in the sun increases your risk of skin cancer and early skin aging. To decrease this risk, regularly use a sunscreen with a Broad Spectrum SPF value of 15 or higher and other sun protection measures including:

● limit time in the sun, especially from 10 a.m. – 2 p.m.

● wear long-sleeved shirts, pants, hats, and sunglasses

● children under 6 months of age: Ask a doctor

Other information

protect the product in this container from excessive heat and direct sun

Inactive ingredients

water, cyclopentasiloxane, alcohol denat., silica, dicaprylyl ether, styrene/acrylates copolymer, PEG-30 dipolyhydroxystearate, dimethicone, cyclohexasiloxane, polymethylsilsesquioxane, glycerin, nylon-12, butylene glycol, caprylyl glycol, citric acid, dicaprylyl carbonate, disodium EDTA, disteardimonium hectorite, fragrance, isostearyl alcohol, lauryl PEG/PPG-18/18 methicone, p-anisic acid, PEG-8 laurate, phenoxyethanol, poly c10-30 alkyl acrylate, potassium sorbate, propylene carbonate, sodium benzoate, sodium chloride, sodium dodecylbenzenesulfonate, tocopherol,
vitis vinifera (grape) fruit extract

Questions or comments?

Call toll free 1-877-378-4249

Monday - Friday (9 a.m. to 5 p.m. EST)